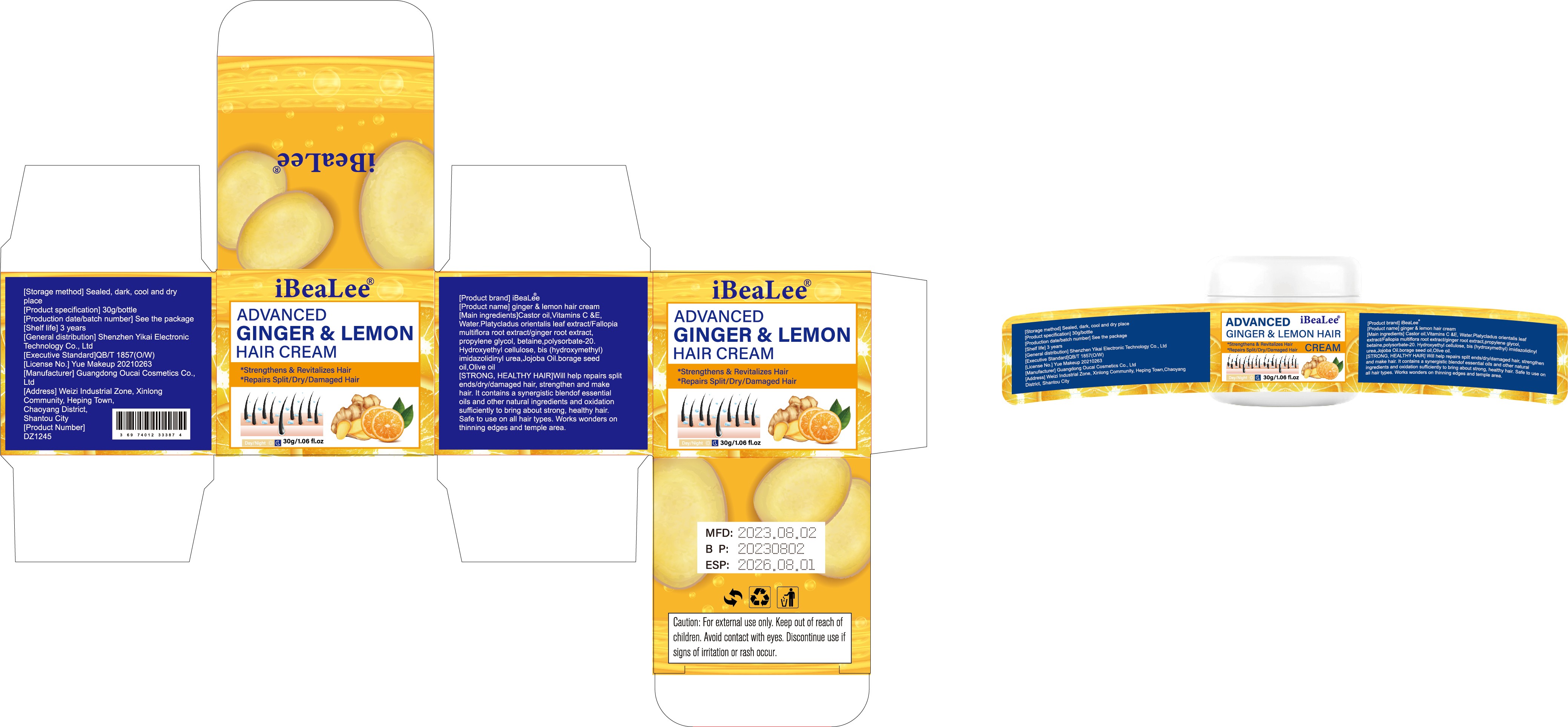 DRUG LABEL: iBeaLee Hair Cream
NDC: 83675-013 | Form: CREAM
Manufacturer: Guangzhou Hanhai Trading Co., Ltd
Category: otc | Type: HUMAN OTC DRUG LABEL
Date: 20230927

ACTIVE INGREDIENTS: CASTOR OIL 2 g/100 g
INACTIVE INGREDIENTS: POLYSORBATE 20; WATER; JOJOBA OIL; ASCORBIC ACID; GINGER; OLIVE OIL; BORAGE OIL; PLATYCLADUS ORIENTALIS LEAF; .ALPHA.-TOCOPHEROL; FALLOPIA MULTIFLORA ROOT; PROPYLENE GLYCOL; HYDROXYETHYL CELLULOSE, UNSPECIFIED; IMIDUREA; BETAINE

Active Ingredient

Castor oil 2%

Purpose

HAIR GROWTH

Use

How to use:
Directions
• Wash and dry your hair. (no wash required if not dirty)
• Take appropriate amount of Ginger Cream, Gently rub, Evenly spread on scalp
• 2-3 times a day.
• Donot wash your hair within 4 hours after using the product Insist at least 1 month.

Warnings

Caution: For external use only. Keep out of reach ofchildren. Avoid contact with eyes. Discontinue useisigns of iritation or rash occur.

Keep Oot Of Reach Of Children

Please store this product out of the reach of children

Do not use

If symptoms such as allergies or itching occur, please stop using this product.

Inactive ingredients

Castor oil,Vitamins C , Vitamins E ,Water.Platycladus orientalis leaf extract/Fallopiamultiflora root extract/ginger root extract,propylene glycol, betaine,polysorbate-20.Hydroxyethyl cellulose, bis (hydroxymethyl)imidazolidinyl urea,Jojoba Oil.borage seedoil,Olive oil

Directions

Apply evenly to hair area